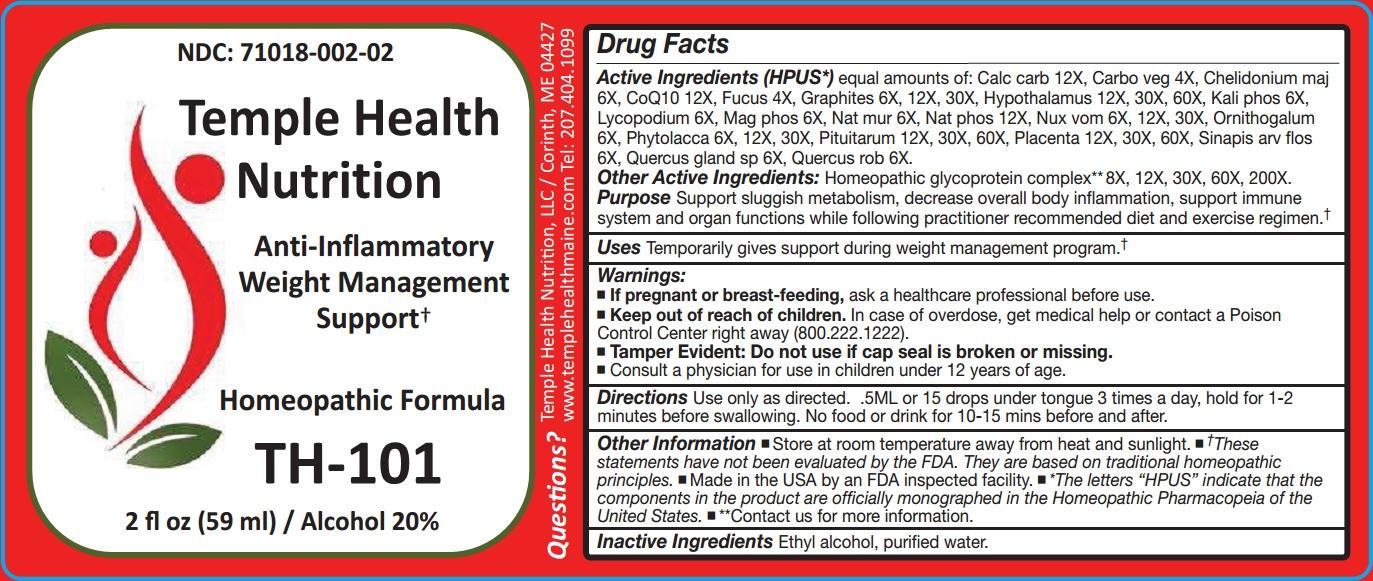 DRUG LABEL: TH-101
NDC: 71018-002 | Form: LIQUID
Manufacturer: Temple Health Nutrition, LLC
Category: homeopathic | Type: HUMAN OTC DRUG LABEL
Date: 20211229

ACTIVE INGREDIENTS: OYSTER SHELL CALCIUM CARBONATE, CRUDE 12 [hp_X]/59 mL; ACTIVATED CHARCOAL 4 [hp_X]/59 mL; CHELIDONIUM MAJUS 6 [hp_X]/59 mL; UBIDECARENONE 12 [hp_X]/59 mL; FUCUS VESICULOSUS 4 [hp_X]/59 mL; GRAPHITE 6 [hp_X]/59 mL; BOS TAURUS HYPOTHALAMUS 12 [hp_X]/59 mL; POTASSIUM PHOSPHATE, DIBASIC 6 [hp_X]/59 mL; LYCOPODIUM CLAVATUM SPORE 6 [hp_X]/59 mL; MAGNESIUM PHOSPHATE, DIBASIC TRIHYDRATE 6 [hp_X]/59 mL; SODIUM CHLORIDE 6 [hp_X]/59 mL; SODIUM PHOSPHATE, DIBASIC, HEPTAHYDRATE 12 [hp_X]/59 mL; STRYCHNOS NUX-VOMICA SEED 6 [hp_X]/59 mL; ORNITHOGALUM UMBELLATUM 6 [hp_X]/59 mL; PHYTOLACCA AMERICANA ROOT 6 [hp_X]/59 mL; SUS SCROFA PITUITARY GLAND 12 [hp_X]/59 mL; SUS SCROFA PLACENTA 12 [hp_X]/59 mL; SINAPIS ARVENSIS FLOWERING/FRUITING TOP 6 [hp_X]/59 mL; QUERCUS ROBUR NUT 6 [hp_X]/59 mL; QUERCUS ROBUR TWIG BARK 6 [hp_X]/59 mL; SUCROSE 8 [hp_X]/59 mL; ARGININE 8 [hp_X]/59 mL; CYSTEINE 8 [hp_X]/59 mL; LEUCINE 8 [hp_X]/59 mL; PROLINE 8 [hp_X]/59 mL; SERINE 8 [hp_X]/59 mL; THREONINE 8 [hp_X]/59 mL; VALINE 8 [hp_X]/59 mL
INACTIVE INGREDIENTS: ALCOHOL; WATER

TH-101

ACTIVE INGREDIENT

Active Ingredients (HPUS*) equal amounts of: Calc carb 12X, Carbo veg 4X, Chelidonium maj 6X, CoQ10 12X, Fucus 4X, Graphites 6X, 12X, 30X, Hypothalamus 12X, 30X, 60X, Kali phos 6X, Lycopodium 6X, Mag phos 6X, Nat mur 6X, Nux vom 6X, 12X, 30X, Ornithogalum 6X, Phytolacca 6X, 12X, 30X, Pituitarum 12X, 30X, 60X, Placenta 12X, 30X, 60X, Sinapis arv flos 6X, Quercus gland sp 6X, Quercus rob 6X.

Other Active Ingredients: Homeopathic glycoprotein complex** 8X, 12X, 30X, 60X, 200X.

Purpose Support sluggish metabolism, decrease overall body inflammation, support immune system and organ functions while following practitioner recommended diet and exercise regimen.†

INDICATIONS AND USAGE

Uses Temporarily gives support during weight management program.†

Warnings:

- If pregnant or breast-feeding, ask a healthcare professional before use.
- Keep out of reach of children. In case of overdose, get medical help or contact a Poison Control Center right away (800.222.1222).
- Tamper Evident: Do not use if cap seal is broken or missing.
- Consult a physician for use in children under 12 years of age.

Keep out of the reach of children.

DOSAGE AND ADMINISTRATION

Directions Use only as directed. .5ML or 15 drops under tongue 3 times a day, hold for 1-2 minutes before swallowing. No food or drink for 10-15 minutes before and after.

Other information

- Store at room temperature away from heat and sunlight.
- †These statements have not been evaluated by the FDA. They are based on traditional homeopathic principles.
- Made in the USA by an FDA inspected facility.
- *The letters "HPUS" indicate that the components in the product are officially monographed in the Homeopathic Pharmacopeia of the United States.
- **Contact us for more information.

Inactive Ingredients Ethyl alcohol, purified water.

Questions?

Temple Health Nutrition, LLC / Corinth, ME 04427

www.templehealthmaine.com Tel: 207.404.1099

PACKAGE LABEL

NDC: 71018-002-02

Temple Health Nutrition

Anti-Inflammatory Weight Management Support†

Homeopathic Formula

TH-101

2 fl oz (59 ml) / Alcohol 20%

PURPOSE

Anti-Inflammatory Weight Management Support